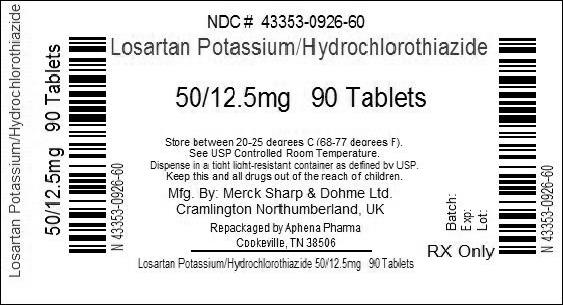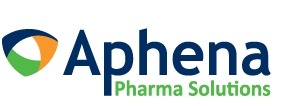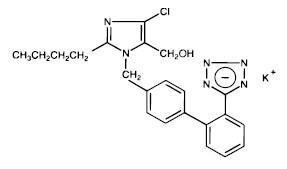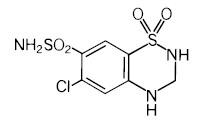 DRUG LABEL: HYZAAR
NDC: 43353-926 | Form: TABLET, FILM COATED
Manufacturer: Aphena Pharma Solutions - Tennessee, LLC
Category: prescription | Type: HUMAN PRESCRIPTION DRUG LABEL
Date: 20140530

ACTIVE INGREDIENTS: losartan potassium 50 mg/1 1; hydrochlorothiazide 12.5 mg/1 1
INACTIVE INGREDIENTS: CELLULOSE, MICROCRYSTALLINE; LACTOSE MONOHYDRATE; STARCH, CORN; magnesium stearate; hydroxypropyl cellulose (type H); HYPROMELLOSES; titanium dioxide; D&C YELLOW NO. 10; ALUMINUM OXIDE; CARNAUBA WAX

HYZAAR® 50/12.5
(LOSARTAN POTASSIUM AND HYDROCHLOROTHIAZIDE TABLETS)
HYZAAR® 100/12.5
(LOSARTAN POTASSIUM AND HYDROCHLOROTHIAZIDE TABLETS)
HYZAAR® 100/25
(LOSARTAN POTASSIUM AND HYDROCHLOROTHIAZIDE TABLETS)

WARNING: FETAL TOXICITY

- When pregnancy is detected, discontinue HYZAAR® as soon as possible.
- Drugs that act directly on the renin-angiotensin system can cause injury and death to the developing fetus. See WARNINGS, Fetal Toxicity.

DESCRIPTION

HYZAAR 50/12.5 (losartan potassium and hydrochlorothiazide), HYZAAR 100/12.5 (losartan potassium and hydrochlorothiazide) and HYZAAR 100/25 (losartan potassium and hydrochlorothiazide) combine an angiotensin II receptor (type AT1) antagonist and a diuretic, hydrochlorothiazide.

Losartan potassium, a non-peptide molecule, is chemically described as 2-butyl-4-chloro-1-[p-(o-1H-tetrazol-5-ylphenyl)benzyl]imidazole-5-methanol monopotassium salt. Its empirical formula is C22H22ClKN6O, and its structural formula is:

Losartan potassium is a white to off-white free-flowing crystalline powder with a molecular weight of 461.01. It is freely soluble in water, soluble in alcohols, and slightly soluble in common organic solvents, such as acetonitrile and methyl ethyl ketone.

Oxidation of the 5-hydroxymethyl group on the imidazole ring results in the active metabolite of losartan.

Hydrochlorothiazide is 6-chloro-3,4-dihydro-2H-1,2,4-benzothiadiazine-7-sulfonamide 1,1-dioxide. Its empirical formula is C7H8ClN3O4S2 and its structural formula is:

Hydrochlorothiazide is a white, or practically white, crystalline powder with a molecular weight of 297.74, which is slightly soluble in water, but freely soluble in sodium hydroxide solution.

HYZAAR is available for oral administration in three tablet combinations of losartan and hydrochlorothiazide. HYZAAR 50/12.5 contains 50 mg of losartan potassium and 12.5 mg of hydrochlorothiazide. HYZAAR 100/12.5 contains 100 mg of losartan potassium and 12.5 mg of hydrochlorothiazide. HYZAAR 100/25 contains 100 mg of losartan potassium and 25 mg of hydrochlorothiazide. Inactive ingredients are microcrystalline cellulose, lactose hydrous, pregelatinized starch, magnesium stearate, hydroxypropyl cellulose, hypromellose, and titanium dioxide. HYZAAR 50/12.5 and HYZAAR 100/25 also contain D&C yellow No. 10 aluminum lake. HYZAAR 50/12.5, HYZAAR 100/12.5, and HYZAAR 100/25 may also contain carnauba wax.

HYZAAR 50/12.5 contains 4.24 mg (0.108 mEq) of potassium, HYZAAR 100/12.5 contains 8.48 mg (0.216 mEq) of potassium, and HYZAAR 100/25 contains 8.48 mg (0.216 mEq) of potassium.

CLINICAL PHARMACOLOGY

Mechanism of Action

Angiotensin II [formed from angiotensin I in a reaction catalyzed by angiotensin converting enzyme (ACE, kininase II)], is a potent vasoconstrictor, the primary vasoactive hormone of the renin-angiotensin system and an important component in the pathophysiology of hypertension. It also stimulates aldosterone secretion by the adrenal cortex. Losartan and its principal active metabolite block the vasoconstrictor and aldosterone-secreting effects of angiotensin II by selectively blocking the binding of angiotensin II to the AT1 receptor found in many tissues (e.g., vascular smooth muscle, adrenal gland). There is also an AT2 receptor found in many tissues but it is not known to be associated with cardiovascular homeostasis. Both losartan and its principal active metabolite do not exhibit any partial agonist activity at the AT1 receptor and have much greater affinity (about 1000-fold) for the AT1 receptor than for the AT2 receptor. In vitro binding studies indicate that losartan is a reversible, competitive inhibitor of the AT1 receptor. The active metabolite is 10 to 40 times more potent by weight than losartan and appears to be a reversible, non-competitive inhibitor of the AT1 receptor.

Neither losartan nor its active metabolite inhibits ACE (kininase II, the enzyme that converts angiotensin I to angiotensin II and degrades bradykinin); nor do they bind to or block other hormone receptors or ion channels known to be important in cardiovascular regulation.

Hydrochlorothiazide is a thiazide diuretic. Thiazides affect the renal tubular mechanisms of electrolyte reabsorption, directly increasing excretion of sodium and chloride in approximately equivalent amounts. Indirectly, the diuretic action of hydrochlorothiazide reduces plasma volume, with consequent increases in plasma renin activity, increases in aldosterone secretion, increases in urinary potassium loss, and decreases in serum potassium. The renin-aldosterone link is mediated by angiotensin II, so coadministration of an angiotensin II receptor antagonist tends to reverse the potassium loss associated with these diuretics.

The mechanism of the antihypertensive effect of thiazides is unknown.

Pharmacokinetics

General

Losartan Potassium

Losartan is an orally active agent that undergoes substantial first-pass metabolism by cytochrome P450 enzymes. It is converted, in part, to an active carboxylic acid metabolite that is responsible for most of the angiotensin II receptor antagonism that follows losartan treatment. The terminal half-life of losartan is about 2 hours and of the metabolite is about 6-9 hours. The pharmacokinetics of losartan and its active metabolite are linear with oral losartan doses up to 200 mg and do not change over time. Neither losartan nor its metabolite accumulate in plasma upon repeated once-daily dosing.

Following oral administration, losartan is well absorbed (based on absorption of radiolabeled losartan) and undergoes substantial first-pass metabolism; the systemic bioavailability of losartan is approximately 33%. About 14% of an orally-administered dose of losartan is converted to the active metabolite. Mean peak concentrations of losartan and its active metabolite are reached in 1 hour and in 3-4 hours, respectively. While maximum plasma concentrations of losartan and its active metabolite are approximately equal, the AUC of the metabolite is about 4 times as great as that of losartan. A meal slows absorption of losartan and decreases its Cmax but has only minor effects on losartan AUC or on the AUC of the metabolite (about 10% decreased).

Both losartan and its active metabolite are highly bound to plasma proteins, primarily albumin, with plasma free fractions of 1.3% and 0.2%, respectively. Plasma protein binding is constant over the concentration range achieved with recommended doses. Studies in rats indicate that losartan crosses the blood-brain barrier poorly, if at all.

Losartan metabolites have been identified in human plasma and urine. In addition to the active carboxylic acid metabolite, several inactive metabolites are formed. Following oral and intravenous administration of ^14C-labeled losartan potassium, circulating plasma radioactivity is primarily attributed to losartan and its active metabolite. In vitro studies indicate that cytochrome P450 2C9 and 3A4 are involved in the biotransformation of losartan to its metabolites. Minimal conversion of losartan to the active metabolite (less than 1% of the dose compared to 14% of the dose in normal subjects) was seen in about one percent of individuals studied.

The volume of distribution of losartan is about 34 liters and of the active metabolite is about 12 liters. Total plasma clearance of losartan and the active metabolite is about 600 mL/min and 50 mL/min, respectively, with renal clearance of about 75 mL/min and 25 mL/min, respectively. When losartan is administered orally, about 4% of the dose is excreted unchanged in the urine and about 6% is excreted in urine as active metabolite. Biliary excretion contributes to the elimination of losartan and its metabolites. Following oral ^14C-labeled losartan, about 35% of radioactivity is recovered in the urine and about 60% in the feces. Following an intravenous dose of ^14C-labeled losartan, about 45% of radioactivity is recovered in the urine and 50% in the feces.

Special Populations

Pediatric: Losartan pharmacokinetics have been investigated in patients 6 to 16 years (see PRECAUTIONS, Pediatric Use).

Geriatric and Gender: Losartan pharmacokinetics have been investigated in the elderly (65-75 years) and in both genders. Plasma concentrations of losartan and its active metabolite are similar in elderly and young hypertensives. Plasma concentrations of losartan were about twice as high in female hypertensives as male hypertensives, but concentrations of the active metabolite were similar in males and females.

Race: Pharmacokinetic differences due to race have not been studied (see also PRECAUTIONS, Race and CLINICAL PHARMACOLOGY, Pharmacodynamics and Clinical Effects, Losartan Potassium, Reduction in the Risk of Stroke, Race).

Renal Insufficiency:

Losartan: Following oral administration, plasma concentrations and AUCs of losartan and its active metabolite are increased by 50-90% in patients with mild (creatinine clearance of 50 to 74 mL/min) or moderate (creatinine clearance 30 to 49 mL/min) renal insufficiency. In this study, renal clearance was reduced by 55-85% for both losartan and its active metabolite in patients with mild or moderate renal insufficiency. Neither losartan nor its active metabolite can be removed by hemodialysis.

Hydrochlorothiazide: Following oral administration, the AUC for hydrochlorothiazide is increased by 70 and 700% for patients with mild and moderate renal insufficiency, respectively. In this study, renal clearance of hydrochlorothiazide decreased by 45 and 85% in patients with mild and moderate renal impairment, respectively.

The usual regimens of therapy with HYZAAR may be followed as long as the patient's creatinine clearance is >30 mL/min. In patients with more severe renal impairment, loop diuretics are preferred to thiazides, so HYZAAR is not recommended. (See DOSAGE AND ADMINISTRATION.)

Hepatic Insufficiency: Following oral administration in patients with mild to moderate alcoholic cirrhosis of the liver, plasma concentrations of losartan and its active metabolite were, respectively, 5 times and about 1.7 times those in young male volunteers. Compared to normal subjects, the total plasma clearance of losartan in patients with hepatic insufficiency was about 50% lower, and the oral bioavailability was about 2 times higher. The lower starting dose of losartan recommended for use in patients with hepatic impairment cannot be given using HYZAAR. Its use in such patients as a means of losartan titration is, therefore, not recommended (see DOSAGE AND ADMINISTRATION).

Drug Interactions

Losartan Potassium

Losartan, administered for 12 days, did not affect the pharmacokinetics or pharmacodynamics of a single dose of warfarin. Losartan did not affect the pharmacokinetics of oral or intravenous digoxin. There is no pharmacokinetic interaction between losartan and hydrochlorothiazide. Coadministration of losartan and cimetidine led to an increase of about 18% in AUC of losartan but did not affect the pharmacokinetics of its active metabolite. Coadministration of losartan and phenobarbital led to a reduction of about 20% in the AUC of losartan and that of its active metabolite. A somewhat greater interaction (approximately 40% reduction in the AUC of active metabolite and approximately 30% reduction in the AUC of losartan) has been reported with rifampin. Fluconazole, an inhibitor of cytochrome P450 2C9, decreased the AUC of the active metabolite by approximately 40%, but increased the AUC of losartan by approximately 70% following multiple doses. Conversion of losartan to its active metabolite after intravenous administration is not affected by ketoconazole, an inhibitor of P450 3A4. The AUC of active metabolite following oral losartan was not affected by erythromycin, another inhibitor of P450 3A4, but the AUC of losartan was increased by 30%.

Hydrochlorothiazide

After oral administration of hydrochlorothiazide, diuresis begins within 2 hours, peaks in about 4 hours and lasts about 6 to 12 hours.

Hydrochlorothiazide is not metabolized but is eliminated rapidly by the kidney. When plasma levels have been followed for at least 24 hours, the plasma half-life has been observed to vary between 5.6 and 14.8 hours. At least 61 percent of the oral dose is eliminated unchanged within 24 hours. Hydrochlorothiazide crosses the placental but not the blood-brain barrier and is excreted in breast milk.

Pharmacodynamics and Clinical Effects

Losartan Potassium

Hypertension

Losartan inhibits the pressor effect of angiotensin II (as well as angiotensin I) infusions. A dose of 100 mg inhibits the pressor effect by about 85% at peak with 25-40% inhibition persisting for 24 hours. Removal of the negative feedback of angiotensin II causes a 2- to 3-fold rise in plasma renin activity and consequent rise in angiotensin II plasma concentration in hypertensive patients. Losartan does not affect the response to bradykinin, whereas ACE inhibitors increase the response to bradykinin. Aldosterone plasma concentrations fall following losartan administration. In spite of the effect of losartan on aldosterone secretion, very little effect on serum potassium was observed.

In a single-dose study in normal volunteers, losartan had no effects on glomerular filtration rate, renal plasma flow or filtration fraction. In multiple-dose studies in hypertensive patients, there were no notable effects on systemic or renal prostaglandin concentrations, fasting triglycerides, total cholesterol or HDL-cholesterol or fasting glucose concentrations. There was a small uricosuric effect leading to a minimal decrease in serum uric acid (mean decrease <0.4 mg/dL) during chronic oral administration.

The antihypertensive effects of losartan were demonstrated principally in 4 placebo-controlled, 6- to 12-week trials of dosages from 10 to 150 mg per day in patients with baseline diastolic blood pressures of 95-115. The studies allowed comparisons of two doses (50-100 mg/day) as once-daily or twice-daily regimens, comparisons of peak and trough effects, and comparisons of response by gender, age, and race. Three additional studies examined the antihypertensive effects of losartan and hydrochlorothiazide in combination.

The 4 studies of losartan monotherapy included a total of 1075 patients randomized to several doses of losartan and 334 to placebo. The 10 and 25 mg doses produced some effect at peak (6 hours after dosing) but small and inconsistent trough (24 hour) responses. Doses of 50, 100, and 150 mg once daily gave statistically significant systolic/diastolic mean decreases in blood pressure, compared to placebo in the range of 5.5-10.5/3.5-7.5 mmHg, with the 150 mg dose giving no greater effect than 50-100 mg. Twice-daily dosing at 50-100 mg/day gave consistently larger trough responses than once-daily dosing at the same total dose. Peak (6 hour) effects were uniformly, but moderately larger than trough effects, with the trough to peak ratio for systolic and diastolic responses 50-95% and 60-90%, respectively.

Analysis of age, gender, and race subgroups of patients showed that men and women, and patients over and under 65, had generally similar responses. Losartan was effective in reducing blood pressure regardless of race, although the effect was somewhat less in Black patients (usually a low-renin population).

The effect of losartan is substantially present within one week but in some studies the maximal effect occurred in 3-6 weeks. In long-term follow-up studies (without placebo control) the effect of losartan appeared to be maintained for up to a year. There is no apparent rebound effect after abrupt withdrawal of losartan. There was essentially no change in average heart rate in losartan-treated patients in controlled trials.

Reduction in the Risk of Stroke

The Losartan Intervention For Endpoint reduction in hypertension (LIFE) study was a multinational, double-blind study comparing losartan and atenolol in 9193 hypertensive patients with ECG-documented left ventricular hypertrophy. Patients with myocardial infarction or stroke within six months prior to randomization were excluded. Patients were randomized to receive once daily losartan 50 mg or atenolol 50 mg. If goal blood pressure (<140/90 mmHg) was not reached, hydrochlorothiazide (12.5 mg) was added first and, if needed, the dose of losartan or atenolol was then increased to 100 mg once daily. If necessary, other antihypertensive treatments (e.g., increase in dose of hydrochlorothiazide therapy to 25 mg or addition of other diuretic therapy, calcium channel blockers, alpha-blockers, or centrally acting agents, but not ACE inhibitors, angiotensin II antagonists, or beta-blockers) were added to the treatment regimen to reach the goal blood pressure.

In efforts to control blood pressure, the patients in both arms of the LIFE study were coadministered hydrochlorothiazide the majority of time they were on study drug (73.9% and 72.4% of days in the losartan and atenolol arms, respectively).

Of the randomized patients, 4963 (54%) were female and 533 (6%) were Black. The mean age was 67 with 5704 (62%) age ≥65. At baseline, 1195 (13%) had diabetes, 1326 (14%) had isolated systolic hypertension, 1469 (16%) had coronary heart disease, and 728 (8%) had cerebrovascular disease. Baseline mean blood pressure was 174/98 mmHg in both treatment groups. The mean length of follow-up was 4.8 years. At the end of study or at the last visit before a primary endpoint, 77% of the group treated with losartan and 73% of the group treated with atenolol were still taking study medication. Of the patients still taking study medication, the mean doses of losartan and atenolol were both about 80 mg/day, and 15% were taking atenolol or losartan as monotherapy, while 77% were also receiving hydrochlorothiazide (at a mean dose of 20 mg/day in each group). Blood pressure reduction measured at trough was similar for both treatment groups but blood pressure was not measured at any other time of the day. At the end of study or at the last visit before a primary endpoint, the mean blood pressures were 144.1/81.3 mmHg for the group treated with losartan and 145.4/80.9 mmHg for the group treated with atenolol [the difference in SBP of 1.3 mmHg was significant (p<0.001), while the difference of 0.4 mmHg in DBP was not significant (p=0.098)].

The primary endpoint was the first occurrence of cardiovascular death, nonfatal stroke, or nonfatal myocardial infarction. Patients with nonfatal events remained in the trial, so that there was also an examination of the first event of each type even if it was not the first event (e.g., a stroke following an initial myocardial infarction would be counted in the analysis of stroke). Treatment with losartan resulted in a 13% reduction (p=0.021) in risk of the primary endpoint compared to the atenolol group; this difference was primarily the result of an effect on fatal and nonfatal stroke. Treatment with losartan reduced the risk of stroke by 25% relative to atenolol (p=0.001).

For additional details on the LIFE study see the label for COZAAR.

Race

In the LIFE study, Black patients treated with atenolol were at lower risk of experiencing the primary composite endpoint compared with Black patients treated with losartan. In the subgroup of Black patients (n=533, 6% of the LIFE study patients), there were 29 primary endpoints among 263 patients on atenolol (11%, 26 per 1000 patient-years) and 46 primary endpoints among 270 patients (17%, 42 per 1000 patient-years) on losartan. This finding could not be explained on the basis of differences in the populations other than race or on any imbalances between treatment groups. In addition, blood pressure reductions in both treatment groups were consistent between Black and non-Black patients. Given the difficulty in interpreting subset differences in large trials, it cannot be known whether the observed difference is the result of chance. However, the LIFE study provides no evidence that the benefits of losartan on reducing the risk of cardiovascular events in hypertensive patients with left ventricular hypertrophy apply to Black patients.

Losartan Potassium and Hydrochlorothiazide

The 3 controlled studies of losartan and hydrochlorothiazide included over 1300 patients assessing the antihypertensive efficacy of various doses of losartan (25, 50 and 100 mg) and concomitant hydrochlorothiazide (6.25, 12.5 and 25 mg). A factorial study compared the combination of losartan/hydrochlorothiazide 50/12.5 mg with its components and placebo. The combination of losartan/hydrochlorothiazide 50/12.5 mg resulted in an approximately additive placebo-adjusted systolic/diastolic response (15.5/9.0 mmHg for the combination compared to 8.5/5.0 mmHg for losartan alone and 7.0/3.0 mmHg for hydrochlorothiazide alone). Another study investigated the dose-response relationship of various doses of hydrochlorothiazide (6.25, 12.5 and 25 mg) or placebo on a background of losartan (50 mg) in patients not adequately controlled (sitting diastolic blood pressure [SiDBP] 93-120 mmHg) on losartan (50 mg) alone. The third study investigated the dose-response relationship of various doses of losartan (25, 50 and 100 mg) or placebo on a background of hydrochlorothiazide (25 mg) in patients not adequately controlled (SiDBP 93-120 mmHg) on hydrochlorothiazide (25 mg) alone. These studies showed an added antihypertensive response at trough (24 hours post-dosing) of hydrochlorothiazide 12.5 or 25 mg added to losartan 50 mg of 5.5/3.5 and 10.0/6.0 mmHg, respectively. Similarly, there was an added antihypertensive response at trough when losartan 50 or 100 mg was added to hydrochlorothiazide 25 mg of 9.0/5.5 and 12.5/6.5 mmHg, respectively. There was no significant effect on heart rate.

There was no difference in response for men and women or in patients over or under 65 years of age.

Black patients had a larger response to hydrochlorothiazide than non-Black patients and a smaller response to losartan. The overall response to the combination was similar for Black and non-Black patients.

Severe Hypertension (Sitting Diastolic Blood Pressure [SiDBP] ≥110 mmHg)

The safety and efficacy of HYZAAR as initial therapy for severe hypertension (defined as a mean SiDBP ≥110 mmHg confirmed on 2 separate occasions off all antihypertensive therapy) was studied in a 6-week double-blind, randomized, multicenter study. Patients were randomized to either losartan and hydrochlorothiazide (50/12.5 mg, once daily) or to losartan (50 mg, once daily) and followed for blood pressure response. Patients were titrated at 2-week intervals if their SiDBP did not reach goal (<90 mmHg). Patients on combination therapy were titrated from losartan 50 mg/hydrochlorothiazide 12.5 mg to losartan 50 mg/hydrochlorothiazide 12.5 mg (sham titration to maintain the blind) to losartan 100 mg/hydrochlorothiazide 25 mg. Patients on monotherapy were titrated from losartan 50 mg to losartan 100 mg to losartan 150 mg, as needed. The primary endpoint was a comparison at 4 weeks of patients who achieved goal diastolic blood pressure (trough SiDBP <90 mmHg).

The study enrolled 585 patients, including 264 (45%) females, 124 (21%) Blacks, and 21 (4%) ≥65 years of age. The mean blood pressure at baseline for the total population was 171/113 mmHg. The mean age was 53 years. After 4 weeks of therapy, the mean SiDBP was 3.1 mmHg lower and the mean SiSBP was 5.6 mmHg lower in the group treated with HYZAAR. As a result, a greater proportion of the patients on HYZAAR reached the target diastolic blood pressure (17.6% for HYZAAR, 9.4% for losartan; p=0.006). Similar trends were seen when the patients were grouped according to gender, race or age (<, ≥ 65).

After 6 weeks of therapy, more patients who received the combination regimen reached target diastolic blood pressure than those who received the monotherapy regimen (29.8% versus 12.5%).

During the study period, there were no reported cases of syncope in either treatment group. There were 2 (0.6%) and 0 (0.0%) cases of hypotension reported in the group treated with HYZAAR and the group treated with losartan, respectively. The overall pattern of adverse events reported for patients treated with HYZAAR as initial therapy was similar to the adverse event profile for patients treated with losartan as initial therapy. For information on the specific adverse events observed during the study period, see ADVERSE REACTIONS, Severe Hypertension.

INDICATIONS AND USAGE

Hypertension

HYZAAR is indicated for the treatment of hypertension. This fixed dose combination is not indicated for initial therapy of hypertension, except when the hypertension is severe enough that the value of achieving prompt blood pressure control exceeds the risk of initiating combination therapy in these patients (see CLINICAL PHARMACOLOGY, Pharmacodynamics and Clinical Effects, and DOSAGE AND ADMINISTRATION).

Hypertensive Patients with Left Ventricular Hypertrophy

HYZAAR is indicated to reduce the risk of stroke in patients with hypertension and left ventricular hypertrophy, but there is evidence that this benefit does not apply to Black patients. (See PRECAUTIONS, Race, CLINICAL PHARMACOLOGY, Pharmacodynamics and Clinical Effects, Losartan Potassium, Reduction in the Risk of Stroke, Race, and DOSAGE AND ADMINISTRATION.)

CONTRAINDICATIONS

HYZAAR is contraindicated in patients who are hypersensitive to any component of this product.

Because of the hydrochlorothiazide component, this product is contraindicated in patients with anuria or hypersensitivity to other sulfonamide-derived drugs.

Do not co-administer aliskiren with HYZAAR in patients with diabetes.

WARNINGS

Fetal Toxicity

Pregnancy Category D

Use of drugs that act on the renin-angiotensin system during the second and third trimesters of pregnancy reduces renal function and increases fetal and neonatal morbidity and death. Resulting oligohydramnios can be associated with fetal lung hypoplasia and skeletal deformations. Potential neonatal adverse effects include skull hypoplasia, anuria, hypotension, renal failure, and death. When pregnancy is detected, discontinue HYZAAR as soon as possible. These adverse outcomes are usually associated with the use of these drugs in the second and third trimester of pregnancy. Most epidemiologic studies examining fetal abnormalities after exposure to antihypertensive use in the first trimester have not distinguished drugs affecting the renin-angiotensin system from other antihypertensive agents. Appropriate management of maternal hypertension during pregnancy is important to optimize outcomes for both mother and fetus.

In the unusual case that there is no appropriate alternative to therapy with drugs affecting the renin-angiotensin system for a particular patient, apprise the mother of the potential risk to the fetus. Perform serial ultrasound examinations to assess the intra-amniotic environment.

If oligohydramnios is observed, discontinue HYZAAR, unless it is considered life-saving for the mother. Fetal testing may be appropriate, based on the week of pregnancy. Patients and physicians should be aware, however, that oligohydramnios may not appear until after the fetus has sustained irreversible injury.

Closely observe infants with histories of in utero exposure to HYZAAR for hypotension, oliguria, and hyperkalemia (see PRECAUTIONS, Pediatric Use).

There was no evidence of teratogenicity in rats or rabbits treated with a maximum losartan potassium dose of 10 mg/kg/day in combination with 2.5 mg/kg/day of hydrochlorothiazide. At these dosages, respective exposures (AUCs) of losartan, its active metabolite, and hydrochlorothiazide in rabbits were approximately 5, 1.5, and 1.0 times those achieved in humans with 100 mg losartan in combination with 25 mg hydrochlorothiazide. AUC values for losartan, its active metabolite and hydrochlorothiazide, extrapolated from data obtained with losartan administered to rats at a dose of 50 mg/kg/day in combination with 12.5 mg/kg/day of hydrochlorothiazide, were approximately 6, 2, and 2 times greater than those achieved in humans with 100 mg of losartan in combination with 25 mg of hydrochlorothiazide. Fetal toxicity in rats, as evidenced by a slight increase in supernumerary ribs, was observed when females were treated prior to and throughout gestation with 10 mg/kg/day losartan in combination with 2.5 mg/kg/day hydrochlorothiazide. As also observed in studies with losartan alone, adverse fetal and neonatal effects, including decreased body weight, renal toxicity, and mortality, occurred when pregnant rats were treated during late gestation and/or lactation with 50 mg/kg/day losartan in combination with 12.5 mg/kg/day hydrochlorothiazide. Respective AUCs for losartan, its active metabolite and hydrochlorothiazide at these dosages in rats were approximately 35, 10 and 10 times greater than those achieved in humans with the administration of 100 mg of losartan in combination with 25 mg hydrochlorothiazide. When hydrochlorothiazide was administered without losartan to pregnant mice and rats during their respective periods of major organogenesis, at doses up to 3000 and 1000 mg/kg/day, respectively, there was no evidence of harm to the fetus.

Thiazides cross the placental barrier and appear in cord blood. There is a risk of fetal or neonatal jaundice, thrombocytopenia, and possibly other adverse reactions that have occurred in adults.

Hypotension — Volume-Depleted Patients

In patients who are intravascularly volume-depleted (e.g., those treated with diuretics), symptomatic hypotension may occur after initiation of therapy with HYZAAR. This condition should be corrected prior to administration of HYZAAR (see DOSAGE AND ADMINISTRATION).

Impaired Hepatic Function

Losartan Potassium and Hydrochlorothiazide

HYZAAR is not recommended for patients with hepatic impairment who require titration with losartan. The lower starting dose of losartan recommended for use in patients with hepatic impairment cannot be given using HYZAAR.

Hydrochlorothiazide

Thiazides should be used with caution in patients with impaired hepatic function or progressive liver disease, since minor alterations of fluid and electrolyte balance may precipitate hepatic coma.

Hypersensitivity Reaction

Hypersensitivity reactions to hydrochlorothiazide may occur in patients with or without a history of allergy or bronchial asthma, but are more likely in patients with such a history.

Systemic Lupus Erythematosus

Thiazide diuretics have been reported to cause exacerbation or activation of systemic lupus erythematosus.

Lithium Interaction

Lithium generally should not be given with thiazides (see PRECAUTIONS, Drug Interactions, Hydrochlorothiazide, Lithium).

Acute Myopia and Secondary Angle-Closure Glaucoma

Hydrochlorothiazide, a sulfonamide, can cause an idiosyncratic reaction, resulting in acute transient myopia and acute angle-closure glaucoma. Symptoms include acute onset of decreased visual acuity or ocular pain and typically occur within hours to weeks of drug initiation. Untreated acute angle-closure glaucoma can lead to permanent vision loss. The primary treatment is to discontinue hydrochlorothiazide as rapidly as possible. Prompt medical or surgical treatments may need to be considered if the intraocular pressure remains uncontrolled. Risk factors for developing acute angle-closure glaucoma may include a history of sulfonamide or penicillin allergy.

PRECAUTIONS

General

Hypersensitivity: Angioedema. See ADVERSE REACTIONS, Postmarketing Experience.

Losartan Potassium and Hydrochlorothiazide

In double-blind clinical trials of various doses of losartan potassium and hydrochlorothiazide, the incidence of hypertensive patients who developed hypokalemia (serum potassium <3.5 mEq/L) was 6.7% versus 3.5% for placebo; the incidence of hyperkalemia (serum potassium >5.7 mEq/L) was 0.4%. No patient discontinued due to increases or decreases in serum potassium. The mean decrease in serum potassium in patients treated with various doses of losartan and hydrochlorothiazide was 0.123 mEq/L. In patients treated with various doses of losartan and hydrochlorothiazide, there was also a dose-related decrease in the hypokalemic response to hydrochlorothiazide as the dose of losartan was increased, as well as a dose-related decrease in serum uric acid with increasing doses of losartan.

Hydrochlorothiazide

Periodic determination of serum electrolytes to detect possible electrolyte imbalance should be performed at appropriate intervals.

All patients receiving thiazide therapy should be observed for clinical signs of fluid or electrolyte imbalance: hyponatremia, hypochloremic alkalosis, and hypokalemia. Serum and urine electrolyte determinations are particularly important when the patient is vomiting excessively or receiving parenteral fluids. Warning signs or symptoms of fluid and electrolyte imbalance, irrespective of cause, include dryness of mouth, thirst, weakness, lethargy, drowsiness, restlessness, confusion, seizures, muscle pains or cramps, muscular fatigue, hypotension, oliguria, tachycardia, and gastrointestinal disturbances such as nausea and vomiting.

Hypokalemia may develop, especially with brisk diuresis, when severe cirrhosis is present, or after prolonged therapy.

Interference with adequate oral electrolyte intake will also contribute to hypokalemia. Hypokalemia may cause cardiac arrhythmia and may also sensitize or exaggerate the response of the heart to the toxic effects of digitalis (e.g., increased ventricular irritability).

Although any chloride deficit is generally mild and usually does not require specific treatment except under extraordinary circumstances (as in liver disease or renal disease), chloride replacement may be required in the treatment of metabolic alkalosis.

Dilutional hyponatremia may occur in edematous patients in hot weather; appropriate therapy is water restriction, rather than administration of salt except in rare instances when the hyponatremia is life-threatening. In actual salt depletion, appropriate replacement is the therapy of choice.

Hyperuricemia may occur or frank gout may be precipitated in certain patients receiving thiazide therapy. Because losartan decreases uric acid, losartan in combination with hydrochlorothiazide attenuates the diuretic-induced hyperuricemia.

In diabetic patients, dosage adjustments of insulin or oral hypoglycemic agents may be required. Hyperglycemia may occur with thiazide diuretics. Thus latent diabetes mellitus may become manifest during thiazide therapy.

The antihypertensive effects of the drug may be enhanced in the postsympathectomy patient.

If progressive renal impairment becomes evident, consider withholding or discontinuing diuretic therapy.

Thiazides have been shown to increase the urinary excretion of magnesium; this may result in hypomagnesemia.

Thiazides may decrease urinary calcium excretion. Thiazides may cause intermittent and slight elevation of serum calcium in the absence of known disorders of calcium metabolism. Marked hypercalcemia may be evidence of hidden hyperparathyroidism. Thiazides should be discontinued before carrying out tests for parathyroid function.

Increases in cholesterol and triglyceride levels may be associated with thiazide diuretic therapy.

Impaired Renal Function

As a consequence of inhibiting the renin-angiotensin-aldosterone system, changes in renal function have been reported in susceptible individuals treated with losartan; in some patients, these changes in renal function were reversible upon discontinuation of therapy.

In patients whose renal function may depend on the activity of the renin-angiotensin-aldosterone system (e.g., patients with severe congestive heart failure), treatment with angiotensin converting enzyme inhibitors has been associated with oliguria and/or progressive azotemia and (rarely) with acute renal failure and/or death. Similar outcomes have been reported with losartan.

In studies of ACE inhibitors in patients with unilateral or bilateral renal artery stenosis, increases in serum creatinine or BUN have been reported. Similar effects have been reported with losartan; in some patients, these effects were reversible upon discontinuation of therapy.

Thiazides should be used with caution in severe renal disease. In patients with renal disease, thiazides may precipitate azotemia. Cumulative effects of the drug may develop in patients with impaired renal function.

Information for Patients

Pregnancy: Female patients of childbearing age should be told about the consequences of exposure to HYZAAR during pregnancy. Discuss treatment options with women planning to become pregnant. Patients should be asked to report pregnancies to their physicians as soon as possible.

Symptomatic Hypotension: A patient receiving HYZAAR should be cautioned that lightheadedness can occur, especially during the first days of therapy, and that it should be reported to the prescribing physician. The patients should be told that if syncope occurs, HYZAAR should be discontinued until the physician has been consulted.

All patients should be cautioned that inadequate fluid intake, excessive perspiration, diarrhea, or vomiting can lead to an excessive fall in blood pressure, with the same consequences of lightheadedness and possible syncope.

Potassium Supplements: A patient receiving HYZAAR should be told not to use potassium supplements or salt substitutes containing potassium without consulting the prescribing physician (see PRECAUTIONS, Drug Interactions, Losartan Potassium).

Drug Interactions

Losartan Potassium

No significant drug-drug pharmacokinetic interactions have been found in interaction studies with hydrochlorothiazide, digoxin, warfarin, cimetidine and phenobarbital. Rifampin, an inducer of drug metabolism, decreased the concentrations of losartan and its active metabolite. (See CLINICAL PHARMACOLOGY, Drug Interactions.) In humans, two inhibitors of P450 3A4 have been studied. Ketoconazole did not affect the conversion of losartan to the active metabolite after intravenous administration of losartan, and erythromycin had no clinically significant effect after oral administration. Fluconazole, an inhibitor of P450 2C9, decreased active metabolite concentration and increased losartan concentration. The pharmacodynamic consequences of concomitant use of losartan and inhibitors of P450 2C9 have not been examined. Subjects who do not metabolize losartan to active metabolite have been shown to have a specific, rare defect in cytochrome P450 2C9. These data suggest that the conversion of losartan to its active metabolite is mediated primarily by P450 2C9 and not P450 3A4.

As with other drugs that block angiotensin II or its effects, concomitant use of potassium-sparing diuretics (e.g., spironolactone, triamterene, amiloride), potassium supplements, or salt substitutes containing potassium may lead to increases in serum potassium (see PRECAUTIONS, Information for Patients, Potassium Supplements).

Lithium: As with other drugs which affect the excretion of sodium, lithium excretion may be reduced. Therefore, serum lithium levels should be monitored carefully if lithium salts are to be co-administered with angiotensin II receptor antagonists.

Non-Steroidal Anti-Inflammatory Drugs (NSAIDs) Including Selective Cyclooxygenase-2 Inhibitors (COX-2 Inhibitors): In patients who are elderly, volume-depleted (including those on diuretic therapy), or with compromised renal function, co-administration of NSAIDs, including selective COX-2 inhibitors, with angiotensin II receptor antagonists (including losartan) may result in deterioration of renal function, including possible acute renal failure. These effects are usually reversible. Monitor renal function periodically in patients receiving losartan and NSAID therapy.

The antihypertensive effect of angiotensin II receptor antagonists, including losartan, may be attenuated by NSAIDs, including selective COX-2 inhibitors.

Dual Blockade of the Renin-Angiotensin System (RAS): Dual blockade of the RAS with angiotensin receptor blockers, ACE inhibitors, or aliskiren is associated with increased risks of hypotension, syncope, hyperkalemia, and changes in renal function (including acute renal failure) compared to monotherapy. Closely monitor blood pressure, renal function, and electrolytes in patients on HYZAAR and other agents that affect the RAS.

Do not co-administer aliskiren with HYZAAR in patients with diabetes. Avoid use of aliskiren with HYZAAR in patients with renal impairment (GFR <60 ml/min).

Hydrochlorothiazide

When administered concurrently, the following drugs may interact with thiazide diuretics:

Alcohol, barbiturates, or narcotics — potentiation of orthostatic hypotension may occur.

Antidiabetic drugs (oral agents and insulin) — dosage adjustment of the antidiabetic drug may be required.

Other antihypertensive drugs — additive effect or potentiation.

Cholestyramine and colestipol resins — Absorption of hydrochlorothiazide is impaired in the presence of anionic exchange resins. Single doses of either cholestyramine or colestipol resins bind the hydrochlorothiazide and reduce its absorption from the gastrointestinal tract by up to 85 and 43 percent, respectively.

Corticosteroids, ACTH, or glycyrrhizin (found in liquorice) — intensified electrolyte depletion, particularly hypokalemia.

Pressor amines (e.g., norepinephrine) — possible decreased response to pressor amines but not sufficient to preclude their use.

Skeletal muscle relaxants, nondepolarizing (e.g., tubocurarine) — possible increased responsiveness to the muscle relaxant.

Lithium — should not generally be given with diuretics. Diuretic agents reduce the renal clearance of lithium and add a high risk of lithium toxicity. Refer to the package insert for lithium preparations before use of such preparations with HYZAAR.

Non-Steroidal Anti-Inflammatory Drugs (NSAIDs) Including Selective Cyclooxygenase-2 Inhibitors (COX-2 Inhibitors) — The administration of a non-steroidal anti-inflammatory agent, including a selective cyclooxygenase-2 inhibitor, can reduce the diuretic, natriuretic, and antihypertensive effects of loop, potassium-sparing and thiazide diuretics. Therefore, when HYZAAR and non-steroidal anti-inflammatory agents, including selective cyclooxygenase-2 inhibitors, are used concomitantly, the patient should be observed closely to determine if the desired effect of the diuretic is obtained.

In patients receiving diuretic therapy, co-administration of NSAIDs with angiotensin receptor blockers, including losartan, may result in deterioration of renal function, including possible acute renal failure. These effects are usually reversible. Monitor renal function periodically in patients receiving hydrochlorothiazide, losartan, and NSAID therapy.

Carcinogenesis, Mutagenesis, Impairment of Fertility

Losartan Potassium and Hydrochlorothiazide

No carcinogenicity studies have been conducted with the losartan potassium and hydrochlorothiazide combination.

Losartan potassium and hydrochlorothiazide when tested at a weight ratio of 4:1 was negative in the Ames microbial mutagenesis assay and the V-79 Chinese hamster lung cell mutagenesis assay. In addition, there was no evidence of direct genotoxicity in the in vitro alkaline elution assay in rat hepatocytes and in vitro chromosomal aberration assay in Chinese hamster ovary cells at noncytotoxic concentrations.

Losartan potassium, coadministered with hydrochlorothiazide, had no effect on the fertility or mating behavior of male rats at dosages up to 135 mg/kg/day of losartan and 33.75 mg/kg/day of hydrochlorothiazide. These dosages have been shown to provide respective systemic exposures (AUCs) for losartan, its active metabolite and hydrochlorothiazide that are approximately 60, 60 and 30 times greater than those achieved in humans with 100 mg of losartan potassium in combination with 25 mg of hydrochlorothiazide. In female rats, however, the coadministration of doses as low as 10 mg/kg/day of losartan and 2.5 mg/kg/day of hydrochlorothiazide was associated with slight but statistically significant decreases in fecundity and fertility indices. AUC values for losartan, its active metabolite and hydrochlorothiazide, extrapolated from data obtained with losartan administered to rats at a dose of 50 mg/kg/day in combination with 12.5 mg/kg/day of hydrochlorothiazide, were approximately 6, 2, and 2 times greater than those achieved in humans with 100 mg of losartan in combination with 25 mg of hydrochlorothiazide.

Losartan Potassium

Losartan potassium was not carcinogenic when administered at maximally tolerated dosages to rats and mice for 105 and 92 weeks, respectively. Female rats given the highest dose (270 mg/kg/day) had a slightly higher incidence of pancreatic acinar adenoma. The maximally tolerated dosages (270 mg/kg/day in rats, 200 mg/kg/day in mice) provided systemic exposures for losartan and its pharmacologically active metabolite that were approximately 160 and 90 times (rats) and 30 and 15 times (mice) the exposure of a 50 kg human given 100 mg per day.

Losartan potassium was negative in the microbial mutagenesis and V-79 mammalian cell mutagenesis assays and in the in vitro alkaline elution and in vitro and in vivo chromosomal aberration assays. In addition, the active metabolite showed no evidence of genotoxicity in the microbial mutagenesis, in vitro alkaline elution, and in vitro chromosomal aberration assays.

Fertility and reproductive performance were not affected in studies with male rats given oral doses of losartan potassium up to approximately 150 mg/kg/day. The administration of toxic dosage levels in females (300/200 mg/kg/day) was associated with a significant (p<0.05) decrease in the number of corpora lutea/female, implants/female, and live fetuses/female at C-section. At 100 mg/kg/day only a decrease in the number of corpora lutea/female was observed. The relationship of these findings to drug-treatment is uncertain since there was no effect at these dosage levels on implants/pregnant female, percent post-implantation loss, or live animals/litter at parturition. In nonpregnant rats dosed at 135 mg/kg/day for 7 days, systemic exposure (AUCs) for losartan and its active metabolite were approximately 66 and 26 times the exposure achieved in man at the maximum recommended human daily dosage (100 mg).

Hydrochlorothiazide

Two-year feeding studies in mice and rats conducted under the auspices of the National Toxicology Program (NTP) uncovered no evidence of a carcinogenic potential of hydrochlorothiazide in female mice (at doses of up to approximately 600 mg/kg/day) or in male and female rats (at doses of up to approximately 100 mg/kg/day). The NTP, however, found equivocal evidence for hepatocarcinogenicity in male mice.

Hydrochlorothiazide was not genotoxic in vitro in the Ames mutagenicity assay of Salmonella typhimurium strains TA 98, TA 100, TA 1535, TA 1537, and TA 1538 and in the Chinese Hamster Ovary (CHO) test for chromosomal aberrations, or in vivo in assays using mouse germinal cell chromosomes, Chinese hamster bone marrow chromosomes, and the Drosophila sex-linked recessive lethal trait gene. Positive test results were obtained only in the in vitro CHO Sister Chromatid Exchange (clastogenicity) and in the Mouse Lymphoma Cell (mutagenicity) assays, using concentrations of hydrochlorothiazide from 43 to 1300 μg/mL, and in the Aspergillus nidulans non-disjunction assay at an unspecified concentration.

Hydrochlorothiazide had no adverse effects on the fertility of mice and rats of either sex in studies wherein these species were exposed, via their diet, to doses of up to 100 and 4 mg/kg, respectively, prior to mating and throughout gestation.

Nursing Mothers

It is not known whether losartan is excreted in human milk, but significant levels of losartan and its active metabolite were shown to be present in rat milk. Thiazides appear in human milk. Because of the potential for adverse effects on the nursing infant, a decision should be made whether to discontinue nursing or discontinue the drug, taking into account the importance of the drug to the mother.

Pediatric Use

Safety and effectiveness of HYZAAR in pediatric patients have not been established.

Neonates with a history of in utero exposure to HYZAAR

If oliguria or hypotension occurs, direct attention toward support of blood pressure and renal perfusion. Exchange transfusions or dialysis may be required as a means of reversing hypotension and/or substituting for disordered renal function.

Geriatric Use

In a controlled clinical study for the reduction in the combined risk of cardiovascular death, stroke and myocardial infarction in hypertensive patients with left ventricular hypertrophy, 2857 patients (62%) were 65 years and over, while 808 patients (18%) were 75 years and over. In an effort to control blood pressure in this study, patients were coadministered losartan and hydrochlorothiazide 74% of the total time they were on study drug. No overall differences in effectiveness were observed between these patients and younger patients. Adverse events were somewhat more frequent in the elderly compared to non-elderly patients for both the losartan and hydrochlorothiazide and the control groups (see CLINICAL PHARMACOLOGY, Special Populations).

Race

In the LIFE study, Black patients with hypertension and left ventricular hypertrophy had a lower risk of stroke on atenolol than on losartan (both cotreated with hydrochlorothiazide in the majority of patients). Given the difficulty in interpreting subset differences in large trials, it cannot be known whether the observed difference is the result of chance. However, the LIFE study does not provide evidence that the benefits of losartan on reducing the risk of cardiovascular events in hypertensive patients with left ventricular hypertrophy apply to Black patients. (See CLINICAL PHARMACOLOGY, Pharmacodynamics and Clinical Effects; Losartan Potassium, Reduction in the Risk of Stroke.)

ADVERSE REACTIONS

Losartan potassium and hydrochlorothiazide has been evaluated for safety in 858 patients treated for essential hypertension and 3889 patients treated for hypertension and left ventricular hypertrophy. In clinical trials with losartan potassium and hydrochlorothiazide, no adverse experiences peculiar to this combination have been observed. Adverse experiences have been limited to those that were reported previously with losartan potassium and/or hydrochlorothiazide. The overall incidence of adverse experiences reported with the combination was comparable to placebo.

In general, treatment with losartan potassium and hydrochlorothiazide was well tolerated. For the most part, adverse experiences have been mild and transient in nature and have not required discontinuation of therapy. In controlled clinical trials, discontinuation of therapy due to clinical adverse experiences was required in only 2.8% and 2.3% of patients treated with the combination and placebo, respectively.

In these double-blind controlled clinical trials, the following adverse experiences reported with losartan and hydrochlorothiazide occurred in ≥1 percent of patients, and more often on drug than placebo, regardless of drug relationship:

Table 1:
 | Losartan Potassium and Hydrochlorothiazide (n=858) | Placebo (n=173)
Body as a Whole Abdominal pain Edema/swelling | 1.2 1.3 | 0.6 1.2
Cardiovascular Palpitation | 1.4 | 0.0
Musculoskeletal Back pain | 2.1 | 0.6
Nervous/Psychiatric Dizziness | 5.7 | 2.9
Respiratory Cough Sinusitis Upper respiratory infection | 2.6 1.2 6.1 | 2.3 0.6 4.6
Skin Rash | 1.4 | 0.0

The following adverse events were also reported at a rate of 1% or greater, but were as, or more, common in the placebo group in studies of essential hypertension: asthenia/fatigue, diarrhea, nausea, headache, bronchitis, pharyngitis.

Adverse events occurred at about the same rates in men and women. Adverse events were somewhat more frequent in the elderly compared to non-elderly patients and somewhat more frequent in Blacks compared to non-Blacks for both the losartan and hydrochlorothiazide and the control groups.

A patient with known hypersensitivity to aspirin and penicillin, when treated with losartan potassium, was withdrawn from study due to swelling of the lips and eyelids and facial rash, reported as angioedema, which returned to normal 5 days after therapy was discontinued.

Superficial peeling of palms and hemolysis were reported in one subject treated with losartan potassium.

Losartan Potassium

Other adverse experiences that have been reported with losartan, without regard to causality, are listed below:

Body as a Whole: chest pain, facial edema, fever, orthostatic effects, syncope; Cardiovascular: angina pectoris, arrhythmias including atrial fibrillation, sinus bradycardia, tachycardia, ventricular tachycardia and ventricular fibrillation, CVA, hypotension, myocardial infarction, second degree AV block; Digestive: anorexia, constipation, dental pain, dry mouth, dyspepsia, flatulence, gastritis, vomiting; General disorders and administration site conditions: malaise; Hematologic: anemia; Metabolic: gout; Musculoskeletal: arm pain, arthralgia, arthritis, fibromyalgia, hip pain, joint swelling, knee pain, leg pain, muscle cramps, muscle weakness, musculoskeletal pain, myalgia, shoulder pain, stiffness; Nervous System/Psychiatric: anxiety, anxiety disorder, ataxia, confusion, depression, dream abnormality, hypesthesia, insomnia, libido decreased, memory impairment, migraine, nervousness, panic disorder, paresthesia, peripheral neuropathy, sleep disorder, somnolence, tremor, vertigo; Respiratory: dyspnea, epistaxis, nasal congestion, pharyngeal discomfort, respiratory congestion, rhinitis, sinus disorder; Skin: alopecia, dermatitis, dry skin, ecchymosis, erythema, flushing, photosensitivity, pruritus, sweating, urticaria; Special Senses: blurred vision, burning/stinging in the eye, conjunctivitis, decrease in visual acuity, taste perversion, tinnitus; Urogenital: impotence, nocturia, urinary frequency, urinary tract infection.

Hydrochlorothiazide

Other adverse experiences that have been reported with hydrochlorothiazide, without regard to causality, are listed below:

Body as a Whole: weakness; Digestive: pancreatitis, jaundice (intrahepatic cholestatic jaundice), sialadenitis, cramping, gastric irritation; Hematologic: aplastic anemia, agranulocytosis, leukopenia, hemolytic anemia, thrombocytopenia; Hypersensitivity: purpura, photosensitivity, urticaria, necrotizing angiitis (vasculitis and cutaneous vasculitis), fever, respiratory distress including pneumonitis and pulmonary edema; Metabolic: hyperglycemia, glycosuria, hyperuricemia; Musculoskeletal: muscle spasm; Nervous System/Psychiatric: restlessness; Renal: renal failure, renal dysfunction, interstitial nephritis; Skin: erythema multiforme including Stevens-Johnson syndrome, exfoliative dermatitis including toxic epidermal necrolysis; Special Senses: transient blurred vision, xanthopsia.

Persistent dry cough (with an incidence of a few percent) has been associated with ACE-inhibitor use and in practice can be a cause of discontinuation of ACE-inhibitor therapy. Two prospective, parallel-group, double-blind, randomized, controlled trials were conducted to assess the effects of losartan on the incidence of cough in hypertensive patients who had experienced cough while receiving ACE-inhibitor therapy. Patients who had typical ACE-inhibitor cough when challenged with lisinopril, whose cough disappeared on placebo, were randomized to losartan 50 mg, lisinopril 20 mg, or either placebo (one study, n=97) or 25 mg hydrochlorothiazide (n=135). The double-blind treatment period lasted up to 8 weeks. The incidence of cough is shown below.

Table 2:
Study 1 [Demographics = (89% Caucasian, 64% female).] | HCTZ | Losartan | Lisinopril
Cough | 25% | 17% | 69%
Study 2 [Demographics = (90% Caucasian, 51% female).] | Placebo | Losartan | Lisinopril
Cough | 35% | 29% | 62%

These studies demonstrate that the incidence of cough associated with losartan therapy, in a population that all had cough associated with ACE-inhibitor therapy, is similar to that associated with hydrochlorothiazide or placebo therapy.

Cases of cough, including positive re-challenges, have been reported with the use of losartan in postmarketing experience.

Severe Hypertension

In a clinical study in patients with severe hypertension (SiDBP ≥110 mmHg), the overall pattern of adverse events reported through six weeks of follow-up was similar in patients treated with HYZAAR as initial therapy and in patients treated with losartan as initial therapy. There were no reported cases of syncope in either treatment group. There were 2 (0.6%) and 0 (0.0%) cases of hypotension reported in the group treated with HYZAAR and the group treated with losartan, respectively. There were 3 (0.8%) and 2 (1.2%) cases of increased serum creatinine (>0.5 mg/dL) in the group treated with HYZAAR and the group treated with losartan, respectively, during the same time period. (See CLINICAL PHARMACOLOGY, Pharmacodynamics and Clinical Effects, Severe Hypertension.)

Postmarketing Experience

The following additional adverse reactions have been reported in postmarketing experience:

Digestive: Hepatitis has been reported rarely in patients treated with losartan.

Hemic: Thrombocytopenia.

Hypersensitivity: Angioedema, including swelling of the larynx and glottis, causing airway obstruction and/or swelling of the face, lips, pharynx, and/or tongue has been reported rarely in patients treated with losartan; some of these patients previously experienced angioedema with other drugs including ACE inhibitors. Vasculitis, including Henoch-Schönlein purpura, has been reported with losartan. Anaphylactic reactions have been reported.

Metabolic and Nutrition: Hyperkalemia, hyponatremia have been reported with losartan.

Musculoskeletal: Rare cases of rhabdomyolysis have been reported in patients receiving angiotensin II receptor blockers.

Respiratory: Dry cough (see above) has been reported with losartan.

Skin: Erythroderma has been reported with losartan.

Laboratory Test Findings

In controlled clinical trials, clinically important changes in standard laboratory parameters were rarely associated with administration of HYZAAR.

Creatinine, Blood Urea Nitrogen: Minor increases in blood urea nitrogen (BUN) or serum creatinine were observed in 0.6 and 0.8 percent, respectively, of patients with essential hypertension treated with HYZAAR alone. No patient discontinued taking HYZAAR due to increased BUN. One patient discontinued taking HYZAAR due to a minor increase in serum creatinine.

Hemoglobin and Hematocrit: Small decreases in hemoglobin and hematocrit (mean decreases of approximately 0.14 grams percent and 0.72 volume percent, respectively) occurred frequently in patients treated with HYZAAR alone, but were rarely of clinical importance. No patients were discontinued due to anemia.

Liver Function Tests: Occasional elevations of liver enzymes and/or serum bilirubin have occurred. In patients with essential hypertension treated with HYZAAR alone, no patients were discontinued due to these laboratory adverse experiences.

Serum Electrolytes: See PRECAUTIONS.

OVERDOSAGE

Losartan Potassium

Significant lethality was observed in mice and rats after oral administration of 1000 mg/kg and 2000 mg/kg, respectively, about 44 and 170 times the maximum recommended human dose on a mg/m^2 basis.

Limited data are available in regard to overdosage in humans. The most likely manifestation of overdosage would be hypotension and tachycardia; bradycardia could occur from parasympathetic (vagal) stimulation. If symptomatic hypotension should occur, supportive treatment should be instituted.

Neither losartan nor its active metabolite can be removed by hemodialysis.

Hydrochlorothiazide

The oral LD50 of hydrochlorothiazide is greater than 10 g/kg in both mice and rats. The most common signs and symptoms observed are those caused by electrolyte depletion (hypokalemia, hypochloremia, hyponatremia) and dehydration resulting from excessive diuresis. If digitalis has also been administered, hypokalemia may accentuate cardiac arrhythmias. The degree to which hydrochlorothiazide is removed by hemodialysis has not been established.

DOSAGE AND ADMINISTRATION

Hypertension

Dosing must be individualized. The usual starting dose of losartan is 50 mg once daily, with 25 mg recommended for patients with intravascular volume depletion (e.g., patients treated with diuretics) (see WARNINGS, Hypotension — Volume-Depleted Patients) and patients with a history of hepatic impairment (see WARNINGS, Impaired Hepatic Function). Losartan can be administered once or twice daily at total daily doses of 25 to 100 mg. If the antihypertensive effect measured at trough using once-a-day dosing is inadequate, a twice-a-day regimen at the same total daily dose or an increase in dose may give a more satisfactory response.

Hydrochlorothiazide is effective in doses of 12.5 to 50 mg once daily and can be given at doses of 12.5 to 25 mg as HYZAAR.

To minimize dose-independent side effects, it is usually appropriate to begin combination therapy only after a patient has failed to achieve the desired effect with monotherapy.

The side effects (see WARNINGS) of losartan are generally rare and apparently independent of dose; those of hydrochlorothiazide are a mixture of dose-dependent (primarily hypokalemia) and dose-independent phenomena (e.g., pancreatitis), the former much more common than the latter. Therapy with any combination of losartan and hydrochlorothiazide will be associated with both sets of dose-independent side effects.

Replacement Therapy: The combination may be substituted for the titrated components.

Dose Titration by Clinical Effect: A patient whose blood pressure is not adequately controlled with losartan monotherapy (see above) or hydrochlorothiazide alone may be switched to HYZAAR 50/12.5 (losartan 50 mg/hydrochlorothiazide 12.5 mg) once daily. If blood pressure remains uncontrolled after about 3 weeks of therapy, the dose may be increased to two tablets of HYZAAR 50/12.5 once daily or one tablet of HYZAAR 100/25 (losartan 100 mg/hydrochlorothiazide 25 mg) once daily. A patient whose blood pressure is not adequately controlled with losartan 100 mg monotherapy (see above) may be switched to HYZAAR 100/12.5 once daily. If blood pressure remains uncontrolled after about 3 weeks of therapy, the dose may be increased to two tablets of HYZAAR 50/12.5 once daily or one tablet of HYZAAR 100/25 (losartan 100 mg/hydrochlorothiazide 25 mg) once daily.

A patient whose blood pressure is inadequately controlled by 25 mg once daily of hydrochlorothiazide, or is controlled but who experiences hypokalemia with this regimen, may be switched to HYZAAR 50/12.5 (losartan 50 mg/hydrochlorothiazide 12.5 mg) once daily, reducing the dose of hydrochlorothiazide without reducing the overall expected antihypertensive response. The clinical response to HYZAAR 50/12.5 should be subsequently evaluated, and if blood pressure remains uncontrolled after about 3 weeks of therapy, the dose may be increased to two tablets of HYZAAR 50/12.5 once daily or one tablet of HYZAAR 100/25 (losartan 100 mg/hydrochlorothiazide 25 mg) once daily.

The usual dose of HYZAAR is one tablet of HYZAAR 50/12.5 once daily. More than two tablets of HYZAAR 50/12.5 once daily or more than one tablet of HYZAAR 100/25 once daily is not recommended. The maximal antihypertensive effect is attained about 3 weeks after initiation of therapy.

Use in Patients with Renal Impairment: The usual regimens of therapy with HYZAAR may be followed as long as the patient's creatinine clearance is greater than 30 mL/min. In patients with more severe renal impairment, loop diuretics are preferred to thiazides, so HYZAAR is not recommended.

Patients with Hepatic Impairment: HYZAAR is not recommended for titration in patients with hepatic impairment (see WARNINGS, Impaired Hepatic Function) because the appropriate 25 mg starting dose of losartan cannot be given.

Severe Hypertension

The starting dose of HYZAAR for initial treatment of severe hypertension is one tablet of HYZAAR 50/12.5 once daily (see CLINICAL PHARMACOLOGY, Pharmacodynamics and Clinical Effects). For patients who do not respond adequately to HYZAAR 50/12.5 after 2 to 4 weeks of therapy, the dosage may be increased to one tablet of HYZAAR 100/25 once daily. The maximum dose is one tablet of HYZAAR 100/25 once daily. HYZAAR is not recommended as initial therapy in patients with hepatic impairment (see WARNINGS, Impaired Hepatic Function) because the appropriate 25 mg starting dose of losartan cannot be given. It is also not recommended for use as initial therapy in patients with intravascular volume depletion (e.g., patients treated with diuretics, see WARNINGS, Hypotension — Volume-Depleted Patients).

Hypertensive Patients with Left Ventricular Hypertrophy

Treatment should be initiated with COZAAR 50 mg once daily. Hydrochlorothiazide 12.5 mg should be added or HYZAAR 50/12.5 substituted if the blood pressure reduction is inadequate. If additional blood pressure reduction is needed, COZAAR 100 mg and hydrochlorothiazide 12.5 mg or HYZAAR 100/12.5 may be substituted, followed by COZAAR 100 mg and hydrochlorothiazide 25 mg or HYZAAR 100/25. For further blood pressure reduction other antihypertensives should be added (see CLINICAL PHARMACOLOGY, Pharmacodynamics and Clinical Effects, Losartan Potassium, Reduction in the Risk of Stroke).

HYZAAR may be administered with other antihypertensive agents.

HYZAAR may be administered with or without food.

HOW SUPPLIED

Repackaged by Aphena Pharma Solutions - TN.
See Repackaging Information for available configurations.

Description | 50 – 12.5 mg | 100 – 12.5 mg | 100 – 25 mg
Product No. | 6517 | 6729 | 6596
Color | Yellow | White | Light Yellow
Shape | Oval | Oval | Oval
Obverse code | Blank | Blank | Blank
Reverse code | 717 | 745 | 747
NDC
Bottle: 30 tablets | 0006-0717-31 | 0006-0745-31 | 0006-0747-31
Bottle: 90 tablets | 0006-0717-54 | 0006-0745-54 | 0006-0747-54
Bottle: 1000 tablets | 0006-0717-82 | 0006-0745-82 | 0006-0747-82

Storage

Store at 25°C (77°F); excursions permitted to 15-30°C (59-86°F) [see USP Controlled Room Temperature]. Keep container tightly closed. Protect from light.

Manuf. for: Merck Sharp & Dohme Corp., a subsidiary of
MERCK & CO., INC., Whitehouse Station, NJ 08889, USA

For patent information: www.merck.com/product/patent/home.html

Copyright © 1995, 2005, 2011, 2013 Merck Sharp & Dohme Corp., a subsidiary of Merck & Co., Inc.
All rights reserved.

Revised: 10/2013

uspi-mk0954a-t-1310r008

Patient Information
HYZAAR®
("HY-zar")
(losartan potassium and hydrochlorothiazide tablets)
50/12.5 mg, 100/12.5 mg, 100/25 mg
Rx only

Read the Patient Information that comes with HYZAAR® before you start taking it and each time you get a refill. There may be new information. This leaflet does not take the place of talking with your doctor about your condition and treatment.

What is the most important information I should know about HYZAAR?

- HYZAAR can cause harm or death to an unborn baby.
- Talk to your doctor about other ways to lower your blood pressure if you plan to become pregnant.
- If you get pregnant while taking HYZAAR tell your doctor right away.

What is HYZAAR?

HYZAAR contains 2 prescription medicines, an angiotensin receptor blocker (ARB) and a diuretic (water pill). It is used to:

- lower high blood pressure (hypertension). HYZAAR is not usually the first medicine used to treat high blood pressure.
- lower the chance of stroke in patients with high blood pressure and a heart problem called left ventricular hypertrophy (LVH). HYZAAR may not help Black patients with this problem.

HYZAAR has not been studied in children less than 18 years old.

High Blood Pressure (hypertension). Blood pressure is the force in your blood vessels when your heart beats and when your heart rests. You have high blood pressure when the force is too much. The losartan ingredient in HYZAAR can help your blood vessels relax so your blood pressure is lower. The hydrochlorothiazide ingredient in HYZAAR works by making your kidneys pass more water and salt.

Left Ventricular Hypertrophy (LVH) is an enlargement of the walls of the left chamber of the heart (the heart's main pumping chamber). LVH can happen from several things. High blood pressure is the most common cause of LVH.

Who should not take HYZAAR?

Do not take HYZAAR if you:

- are allergic to any ingredients in HYZAAR. See a complete list of ingredients in HYZAAR at the end of this leaflet.
- are allergic to any sulfonamide-containing ("sulfa") medicines. Ask your doctor if you are not sure what sulfonamide-containing ("sulfa") medicines are.
- are not passing urine.
- have diabetes and are taking a medicine called aliskiren to reduce blood pressure.

What should I tell my doctor before taking HYZAAR?

Tell your doctor about all your medical conditions including if you:

- are pregnant or planning to become pregnant. See "What is the most important information I should know about HYZAAR?"
- are breastfeeding or plan to breastfeed. HYZAAR can pass into your milk and may harm your baby. You and your doctor should decide if you will take HYZAAR or breastfeed. You should not do both.
- have been vomiting (throwing up), having diarrhea, sweating a lot, or not drinking enough fluids. These could cause you to have low blood pressure.
- have liver problems
- have kidney problems
- have systemic lupus erythematosus (Lupus; SLE)
- have diabetes
- have asthma
- have gout
- have any allergies

Tell your doctor about all of the medicines you take, including prescription and non-prescription medicines, vitamins, and herbal supplements.

HYZAAR and certain other medicines may interact with each other. Especially tell your doctor if you are taking:

- potassium supplements
- salt substitutes containing potassium
- water pills (diuretics)
- lithium (a medicine used to treat a certain kind of depression)
- medicines used to treat pain and arthritis, called non-steroidal anti-inflammatory drugs (NSAIDs), including COX-2 inhibitors
- other medicines to reduce blood pressure.

Know the medicines you take. Keep a list of your medicines and show it to your doctor and pharmacist when you get a new medicine.

How should I take HYZAAR?

- Take HYZAAR exactly as prescribed by your doctor. Your doctor may change your dose if needed.
- HYZAAR can be taken with or without food.
- If you miss a dose, take it as soon as you remember. If it is close to your next dose, do not take the missed dose. Just take the next dose at your regular time.
- If you take too much HYZAAR, call your doctor or Poison Control Center, or go to the nearest hospital emergency room right away.
- Your doctor may do blood tests from time to time while you are taking HYZAAR.

What are the possible side effects of HYZAAR?

HYZAAR may cause the following side effects that may be serious:

- Injury or death of unborn babies. See "What is the most important information I should know about HYZAAR?"
- Allergic reaction. Symptoms of an allergic reaction are swelling of the face, lips, throat, or tongue. Get emergency medical help right away and stop taking HYZAAR.
- Low blood pressure (hypotension). Low blood pressure may cause you to feel faint or dizzy. Lie down if you feel faint or dizzy. Call your doctor right away.
- A new or worsening condition called systemic lupus erythematosus (Lupus; SLE)
- If you have kidney problems, you may see a worsening in how well your kidneys work. Call your doctor if you get swelling in your feet, ankles, or hands, or unexplained weight gain.
- If you have liver problems, you may see a worsening in how well your liver works. Call your doctor if you get nausea, pain in the right upper stomach area (abdomen), yellow eyes or skin (which can be itchy).
- Eye problems. One of the medicines in HYZAAR can cause eye problems that, if left untreated, may lead to vision loss. Symptoms of eye problems can happen within hours to weeks of starting HYZAAR. Tell your doctor right away if you have:
  - decrease in vision
  - eye pain

The most common side effects of HYZAAR in people with high blood pressure are:

- "colds" (upper respiratory infection)
- dizziness
- stuffy nose
- back pain
- fast or irregular heartbeat (palpitations)
- rash

Tell your doctor if you get any side effect that bothers you or that won't go away. This is not a complete list of side effects. For a complete list, ask your doctor or pharmacist.

How should I store HYZAAR?

- Store HYZAAR at room temperature at 59°F to 86°F (15°C to 30°C).
- Keep HYZAAR in a tightly closed container, and keep HYZAAR out of the light.
- Keep HYZAAR and all medicines out of the reach of children.

General information about HYZAAR

Medicines are sometimes prescribed for conditions that are not mentioned in patient information leaflets. Do not use HYZAAR for a condition for which it was not prescribed. Do not give HYZAAR to other people, even if they have the same symptoms that you have. It may harm them.

This leaflet summarizes the most important information about HYZAAR. If you would like more information, talk with your doctor. You can ask your pharmacist or doctor for information that is written for health professionals.

What are the ingredients in HYZAAR?

Active ingredients: losartan potassium, hydrochlorothiazide

Inactive ingredients:

microcrystalline cellulose, lactose hydrous, pregelatinized starch, magnesium stearate, hydroxypropyl cellulose, hypromellose, titanium dioxide. HYZAAR 50/12.5 and HYZAAR 100/25 also contain D&C yellow No. 10 aluminum lake.

HYZAAR 50/12.5, HYZAAR 100/12.5, and HYZAAR 100/25 may also contain carnauba wax.

Manuf. for: Merck Sharp & Dohme Corp., a subsidiary of
MERCK & CO., INC., Whitehouse Station, NJ 08889, USA

For patent information: www.merck.com/product/patent/home.html

Copyright © 2006, 2011, 2013 Merck Sharp & Dohme Corp., a subsidiary of Merck & Co., Inc.
All rights reserved.

Revised: 10/2013

usppi-mk0954a-t-1310r008

Repackaging Information

Please reference the How Supplied section listed above for a description of individual tablets or capsules. This drug product has been received by Aphena Pharma - TN in a manufacturer or distributor packaged configuration and repackaged in full compliance with all applicable cGMP regulations. The package configurations available from Aphena are listed below:

Count | 50/12.5mg
90 | 43353-926-60

Store between 20°-25°C (68°-77°F). See USP Controlled Room Temperature. Dispense in a tight light-resistant container as defined by USP. Keep this and all drugs out of the reach of children.

Repackaged by:
Cookeville, TN 38506
20140530SC

PRINCIPAL DISPLAY PANEL - 50/12.5mg

NDC 4333-926 - Losartan Potassium/Hydrochlorothiazide 50/12.5mg - Rx Only